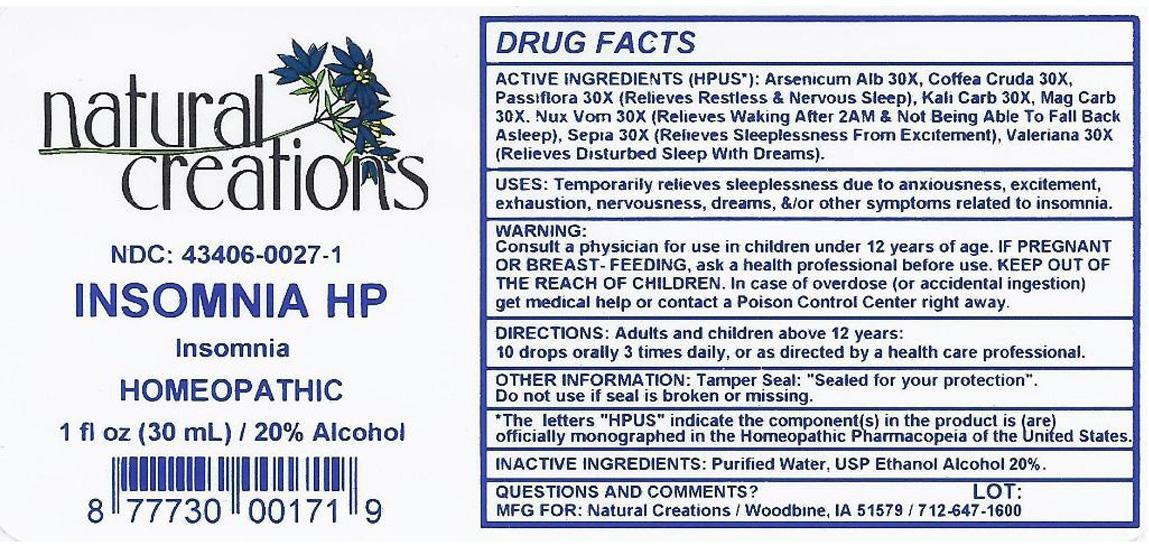 DRUG LABEL: INSOMNIA HP
NDC: 43406-0027 | Form: LIQUID
Manufacturer: Natural Creations, Inc.
Category: homeopathic | Type: HUMAN OTC DRUG LABEL
Date: 20121105

ACTIVE INGREDIENTS: ARSENIC TRIOXIDE 30 [hp_X]/1 mL; ARABICA COFFEE BEAN 30 [hp_X]/1 mL; POTASSIUM CARBONATE 30 [hp_X]/1 mL; MAGNESIUM CARBONATE 30 [hp_X]/1 mL; STRYCHNOS NUX-VOMICA SEED 30 [hp_X]/1 mL; PASSIFLORA INCARNATA TOP 30 [hp_X]/1 mL; SEPIA OFFICINALIS JUICE 30 [hp_X]/1 mL; VALERIAN 30 [hp_X]/1 mL
INACTIVE INGREDIENTS: WATER; ALCOHOL

INSOMNIA HP

ACTIVE INGREDIENT

ACTIVE INGREDIENTS (HPUS*): Arsenicum Album 30X, Coffea Cruda 30X, Kali Carbonica 30X, Magnesia Carbonica 30X, Nux Vomica 30X, Passiflora Incarnata 30X, Sepia 30X, Valeriana Officinalis 30X

INDICATIONS AND USAGE

USES: Temporarily relieves sleeplessness due to anxiousness, excitement, exhaustion, nervousness, dreams, &/or other symptoms related to insomnia.

WARNING:

Consult a physician for use in children under 12 years of age. IF PREGNANT OR BREAST-FEEDING, ask a health care professional before use. KEEP OUT OF THE REACH OF CHILDREN. In case of overdose (or accidental ingestion) get medical help or contact a Poison Control Center.

DOSAGE AND ADMINISTRATION

DIRECTIONS: Adults and children above 12 years: 10 drops orally 3 times daily, or as directed by a health care professional.

OTHER INFORMATION: Tamper Seal: "Sealed for your protection."

Do not use if seal is broken or missing.

REFERENCES

*The letters "HPUS" indicate the components in the product are officially monographed in the Homeopathic Pharmacopeia of the United States.

INACTIVE INGREDIENTS: Purified Water, USP Ethanol Alcohol 20%

QUESTIONS AND COMMENTS?

MFG FOR: Natural Creations / Woodbine, IA / 51579 712.647.1600

LOT:

PURPOSE

USES: Temporarily relieves sleeplessness due to anxiousness, excitement, exhaustion, nervousness, dreams, &/or other symptoms related to insomnia.

KEEP OUT OF REACH OF CHILDREN

KEEP OUT OF THE REACH OF CHILDREN. In case of overdose (or accidental ingestion) get medical help or contact a Poison Control Center.

PACKAGE LABEL

NDC: 43406-0027-1

INSOMNIA HP

Insomnia

HOMEOPATHIC

1 fl oz (30 mL) / 20% Alcohol

UPC: 877730001719